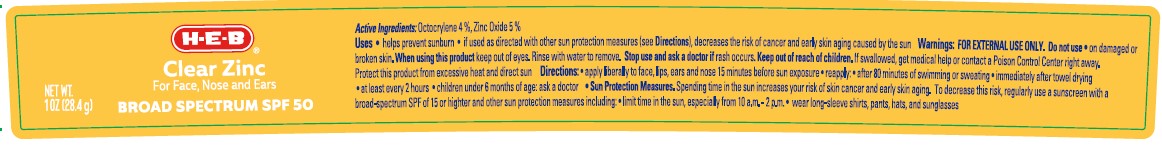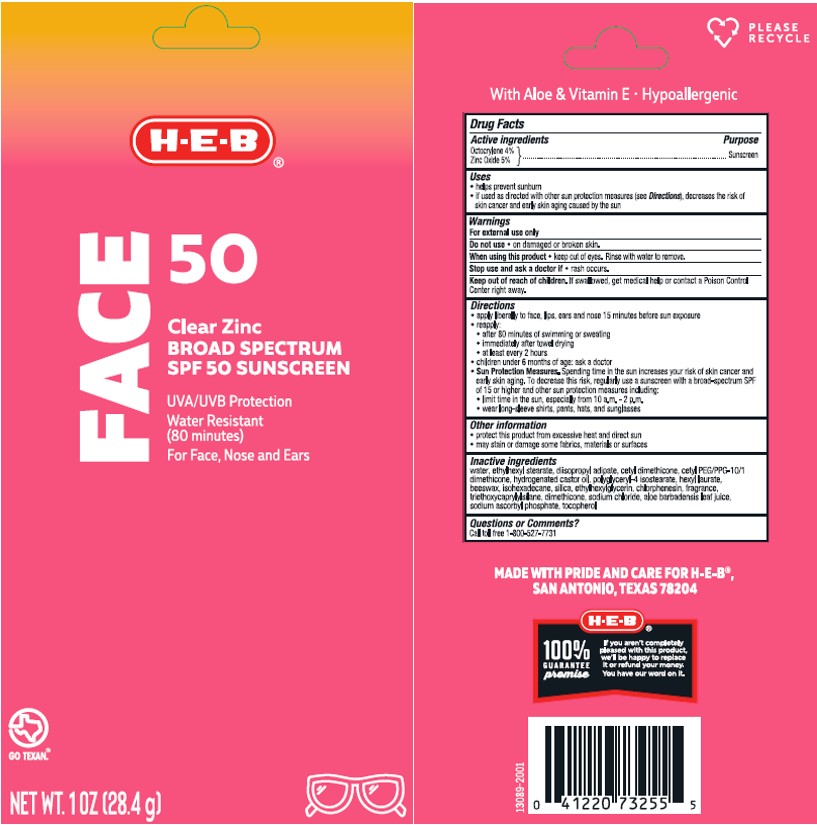 DRUG LABEL: HEB Face 50 Clear Zinc Sunscreen
NDC: 37808-151 | Form: LOTION
Manufacturer: H.E.B.
Category: otc | Type: HUMAN OTC DRUG LABEL
Date: 20241015

ACTIVE INGREDIENTS: ZINC OXIDE 50 mg/1 g; OCTOCRYLENE 40 mg/1 g
INACTIVE INGREDIENTS: CETYL PEG/PPG-10/1 DIMETHICONE (HLB 5); ISOHEXADECANE; ETHYLHEXYL STEARATE; ALOE VERA LEAF; HEXYL LAURATE; CETYL DIMETHICONE 45; DIISOPROPYL ADIPATE; WHITE WAX; CHLORPHENESIN; HEXAMETHYLDISILOXANE; HYDROGENATED CASTOR OIL; POLYGLYCERYL-4 ISOSTEARATE; SODIUM ASCORBYL PHOSPHATE; SODIUM CHLORIDE; .ALPHA.-TOCOPHEROL, DL-; WATER; SILICON DIOXIDE; ETHYLHEXYLGLYCERIN; TRIETHOXYCAPRYLYLSILANE

HEB Face 50 Clear Zinc Sunscreen Lotion

Active ingredients

Octocrylene 4.0%, Zinc Oxide 5.0%

Purpose

Sunscreen

Uses

• helps prevent sunburn • if used as directed with other sun protection measures (see Directions), decreases the risk of skin cancer and early skin aging caused by the sun

Warnings

For external use only

Do not use

• on damaged or broken skin

When using this product

• keep out of eyes. Rinse with water to remove.

Stop use and ask a doctor if

- rash occurs

Keep out of reach of children.

If swallowed, get medical help or contact a Poison Control Center right away.

Directions

• apply liberally 15 minutes before sun exposure

• reapply:

• after 80 minutes of swimming or sweating

• immediately after towel drying

• at least every 2 hours

• children under 6 months of age: Ask a doctor

- Sun Protection Measures. Spending time in the sun increases your risk of skin cancer and early skin aging. To decrease this risk, regularly use a sunscreen with a Broad Spectrum SPF value of 15 or higher and other sun protection measures including:

• limit time in the sun, especially from 10 a.m. - 2 p.m.

• wear long-sleeved shirts, pants, hats, and sunglasses

Other information

• protect the product in this container from excessive heat and direct sun

• may stain or damage some fabrics, materials or surfaces

Inactive ingredients

Water, Ethylhexyl Stearate, Diisopropyl Adipate, Cetyl Dimethicone, Cetyl PEG/PPG-10/1 Dimethicone, Hydrogenated Castor Oil, Polyglyceryl-4 Isostearate, Hexyl Laurate, Beeswax, Isohexadecane, Silica, Ethylhexylglycerin, Chlorphenesin, Fragrance, Triethoxycaprylylsilane, Dimethicone, Sodium Chloride, Aloe Barbadensis Leaf Juice, Sodium Ascorbyl Phosphate, Tocopherol.